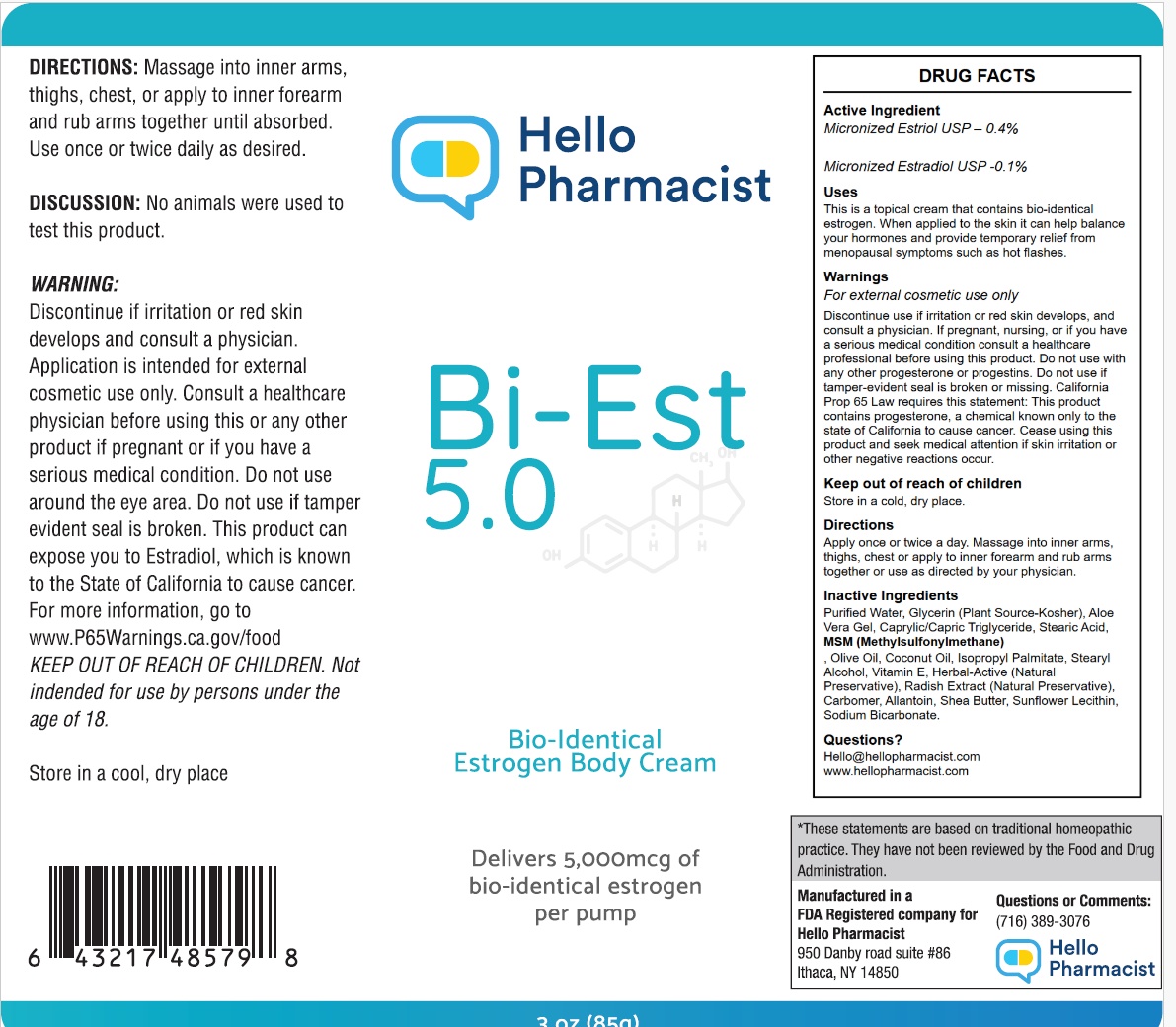 DRUG LABEL: HelloPharmacist Bi-EST 5.0 Cream
NDC: 85838-0211 | Form: CREAM
Manufacturer: Nutrition Unlimited INC
Category: otc | Type: HUMAN OTC DRUG LABEL
Date: 20250705

ACTIVE INGREDIENTS: ESTRIOL 4 mg/85 g; ESTRADIOL 1 mg/85 g
INACTIVE INGREDIENTS: GLYCERIN; SHEA BUTTER; SODIUM BICARBONATE; OLIVE OIL; ALOE VERA LEAF; ISOPROPYL PALMITATE; ALLANTOIN; LECITHIN, SUNFLOWER; STEARIC ACID; COCONUT OIL

DRUG FACTS

Active Ingredients

Micronized Estriol USP (Wild Yam) .4%

Micronized Estradiol USP (Wild Yam) .1%

PURPOSE

This is a topical cream that contains bio-identical estriol and estradiol derived from wild yam and formulated in an 80:20 ratio. When applied to the skin it can help balance your hormones and provide temporary relief from menopausal symptoms such as hot flashes.

USES:

This is a topical cream that contains bio-identical estriol and estradiol derived from wild yam and formulated in an 80:20 ratio. When applied to the skin it can help balance your hormones and provide temporary relief from menopausal symptoms such as hot flashes.

DIRECTIONS: Apply once or twice a day. Massage into inner arms, thighs, chest or apply to inner forearm and rub arms together or use as directed by your Physician.

WARNINGS

For external cosmetic use only. If pregnant or nursing, consult a healthcare professional before using this product. Cease using this product and seek medical attention if skin irritation or other negative reactions occur. Do not use if tamper-evident seal is broken or missing.

California Prop 65 Law requires this statement:

This product contains estrogen, a chemical known only to the state of California to cause cancer.

KEEP OUT OF REACH OF CHILDREN.

PREGNANCY

If pregnant or nursing or if you have a serious medical condition consult a healthcare professional before using this product.

Keep Out of Reach of Children.

DOSAGE AND ADMINISTRATION

Apply once or twice a day. Massage into inner arms, thighs, chest or apply to inner forearm and rub arms together or use as directed by you physician.

INACTIVE INGREDIENT

Purified Water, Vegetable Glycerin, Aloe Vera Gel,
Caprylic/Capric Triglyceride,Stearic Acid,Olive Oil,
Coconut Oil, Shea Butter, Sunflower Lecithin,
Methylsulfonylmethane (MSM), Stearyl Alcohol,
Isopropyl Palmitate,Allantoin,Carbomer,
Sodium Bicarbonate, Herbal-Active
(Natural Preservstive)

Questions?

Hello@HelloPharmacist.com

HelloPharmacist.com